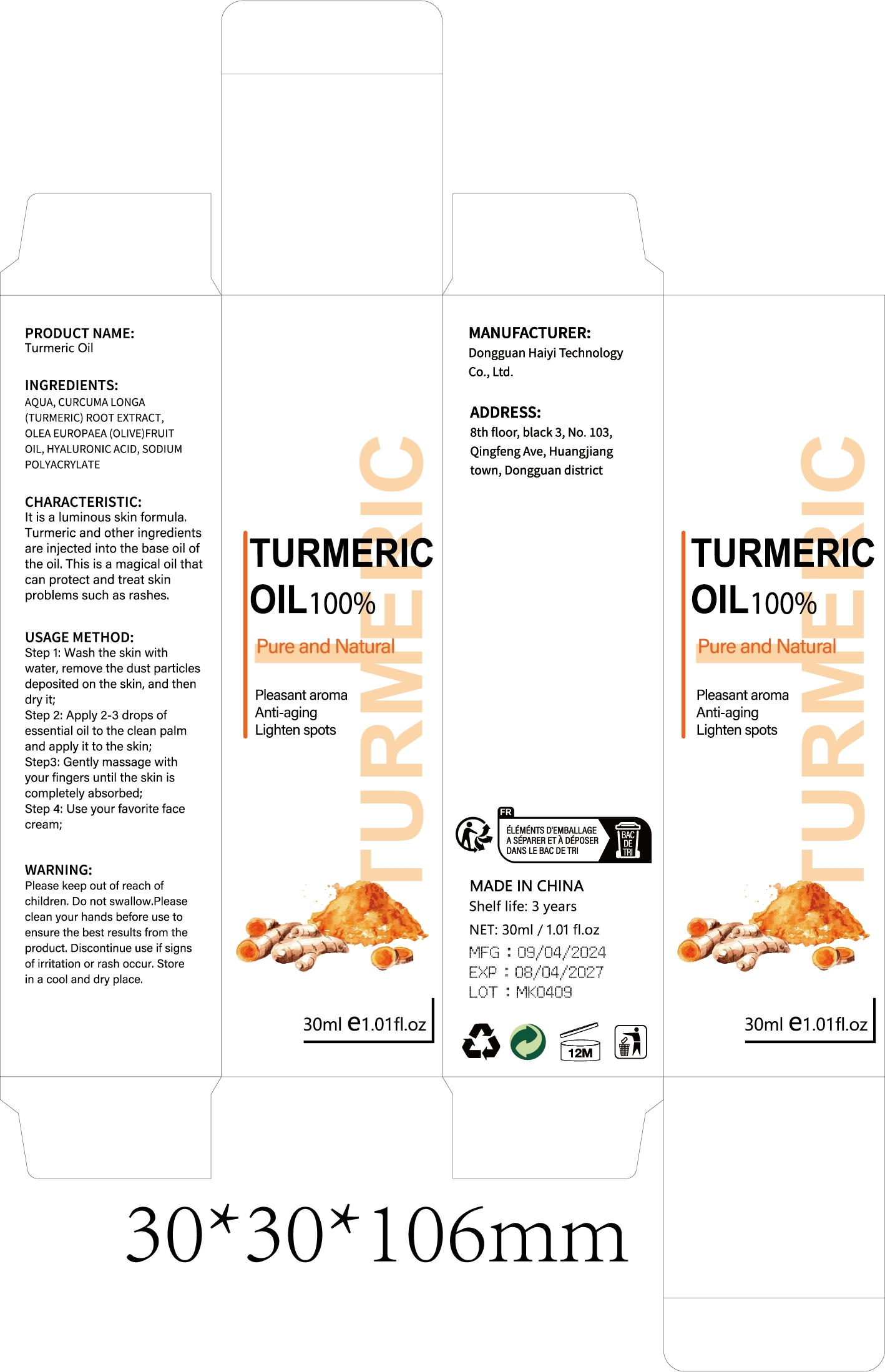 DRUG LABEL: Turmeric Oil
NDC: 84732-006 | Form: LIQUID
Manufacturer: Dongguan Haiyi Technology Co.,Ltd.
Category: otc | Type: HUMAN OTC DRUG LABEL
Date: 20240923

ACTIVE INGREDIENTS: WATER 1 mg/30 mL
INACTIVE INGREDIENTS: HYDROGENATED OLIVE OIL; TURMERIC; SODIUM POLYACRYLATE (2500000 MW); HYALURONIC ACID

Active ingredient

AQUA

Inactive ingredient

CURCUMA LONGA (TURMERIC) ROOT EXTRACT,

OLEA EUROPAEA (OLIVE) FRUIT OIL,

HYALURONIC ACID,

SODIUM POLYACRYLATE

Purpose section

It is a luminous skin formula.Turmeric and other ingredientsare injected into the base oil of the oil. This is a magical oil that can protect and treat skin problems such as rashes.

Warning

Please keep out of reach of children. Do not swallow.Please clean your hands before use toensure the best results from the product. Discontinue use if signsof irritation or rash occur. Storein a cool and dry place.

stop use

This product may cause allergic reactions in asmall number of people.
lf youexperience any discomfort,please stop using it immediately.

not use

Not suitable for use by children, pregnantor breastfeeding people.

OUT OF CHILDREN

KEEP THE PRODUCT OUT OF REACH OF CHILDREN to

HOW TO USE

Step 1: Wash the skin withwater, remove the dust particlesdeposited on the skin, and thendry it;

Step 2: Apply 2-3 drops ofessential oil to the clean palmand apply it to the skin;

Step3: Gently massage withyour fingers until the skin iscompletely absorbed;

Step 4: Use your favorite facecream;

Dosage

take an appropriateamount,Use 2-3 times a week